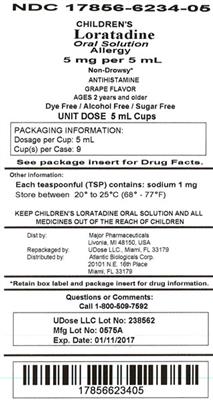 DRUG LABEL: Loratadine
                                    
NDC: 17856-6234 | Form: SOLUTION
Manufacturer: Atlantic Biologicals Corps
Category: otc | Type: HUMAN OTC DRUG LABEL
Date: 20160816

ACTIVE INGREDIENTS: Loratadine 5 mg/5 mL
INACTIVE INGREDIENTS: anhydrous citric acid; butylated hydroxyanisole; glycerin; propylene glycol; sodium benzoate; sucralose; water

Children's Loratadine Oral Solution

Active Ingredient: Loratadine 5 mg (in each 5 mL(teaspoonful)(TSP))

Purpose: Antihistamine

Uses

temporarily relieves these symptoms due to hay fever or other upper respiratory allergies:

- runny nose
- itchy, watery eyes
- sneezing
- itching of the nose or throat

Warnings

ever had allergic reaction to this product or any of it's ingredients Do not use if you have

ASK DOCTOR

liver or kidney disease. Your doctor should determine if you need a different dose. Ask a doctor before use if you have

WHEN USING

do not take more than directed. Taking more than directed may cause drowsiness. When using this product

STOP USE

an allergic reaction to this product occurs. Seek medical help right away. Stop use and ask a doctor if

PREGNANCY OR BREAST FEEDING

, ask a health professional before use. If pregnant or breast-feeding

KEEP OUT OF REACH OF CHILDREN

. In case of overdose, get medical help or contact a Poison Control Center right away. Keep out of reach of children

Directions

adults and children 6 years and over | 2 teaspoonfuls (TSP) daily; do not take more than 2 teaspoonfuls (TSP) in 24 hours
children 2 to under 6 years of age | 1 teaspoonful (TSP) daily; do not take more than 1 teaspoonful (TSP) in 24 hours
children under 2 years of age | ask a doctor
consumers with liver or kidney disease | ask a doctor

Other information

- : sodium 1 mg Each teaspoonful contains
- Safety Sealed. Do not use if imprinted seal around cap is broken or missing
- Store between 20° to 25°C (68° to 77°F)

Inactive ingredients

Butylated hydroxylanisole, citric acid, glycerin, grape flavor, propylene glycol, purified water, sodium benzoate, sucralose.

Questions

1-800-616-2471

Distributed by: Major Pharmaceuticals 31778 Enterprise Drive, Livonia, MI 48150 USA